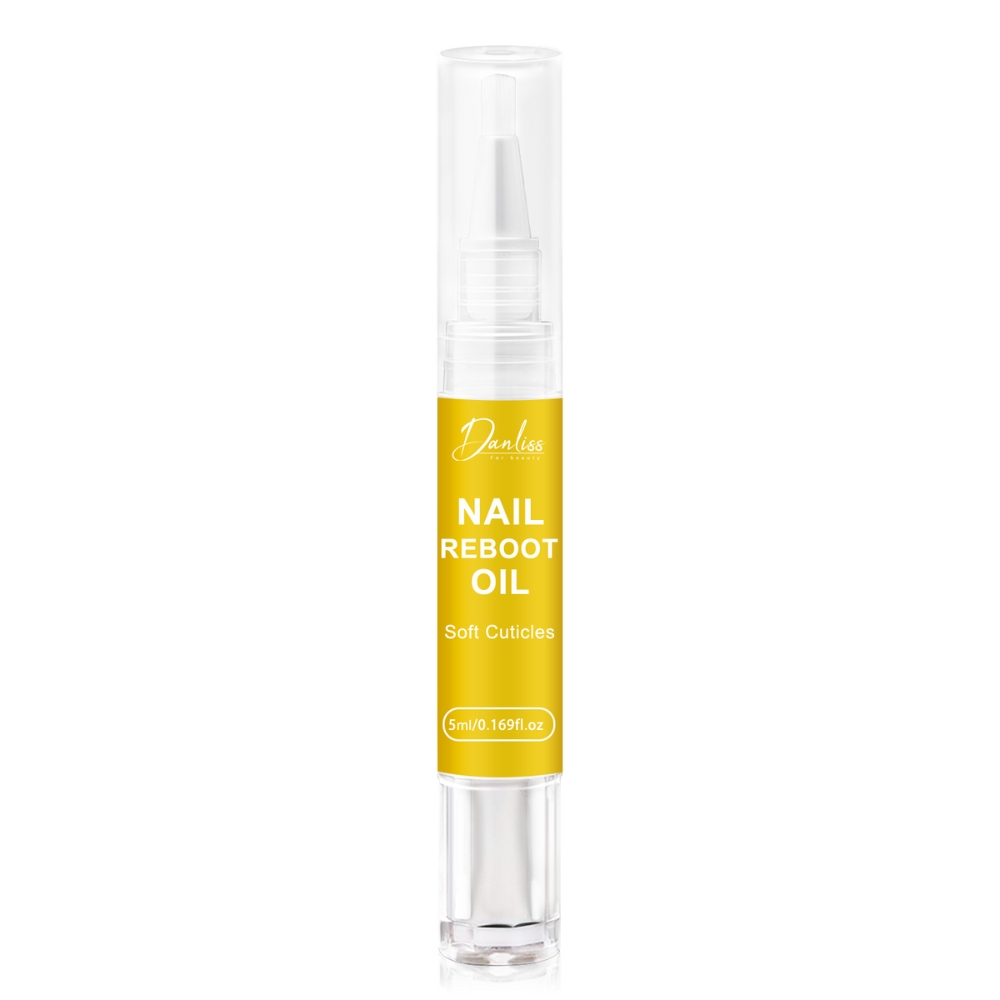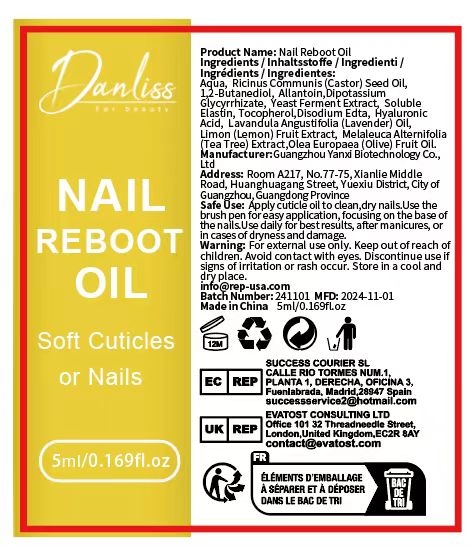 DRUG LABEL: Nail Reboot Oil
NDC: 84025-280 | Form: CREAM
Manufacturer: Guangzhou Yanxi Biotechnology Co., Ltd
Category: otc | Type: HUMAN OTC DRUG LABEL
Date: 20241216

ACTIVE INGREDIENTS: ALLANTOIN 2 mg/5 mL; RICINUS COMMUNIS (CASTOR) SEED OIL 3 mg/5 mL
INACTIVE INGREDIENTS: WATER

DOSAGE AND ADMINISTRATION

Apply cuticle oil to clean,dry nails.Use the brush pen for easy application, focusing on the base of the nails.Use daily for best results, after manicures, or in cases of dryness and damage.

WARNINGS

Keep out of children

INACTIVE INGREDIENT

Aqua

INDICATIONS AND USAGE

For daily nail care

Keep out of children

PURPOSE

Soft Cuticles or Nails